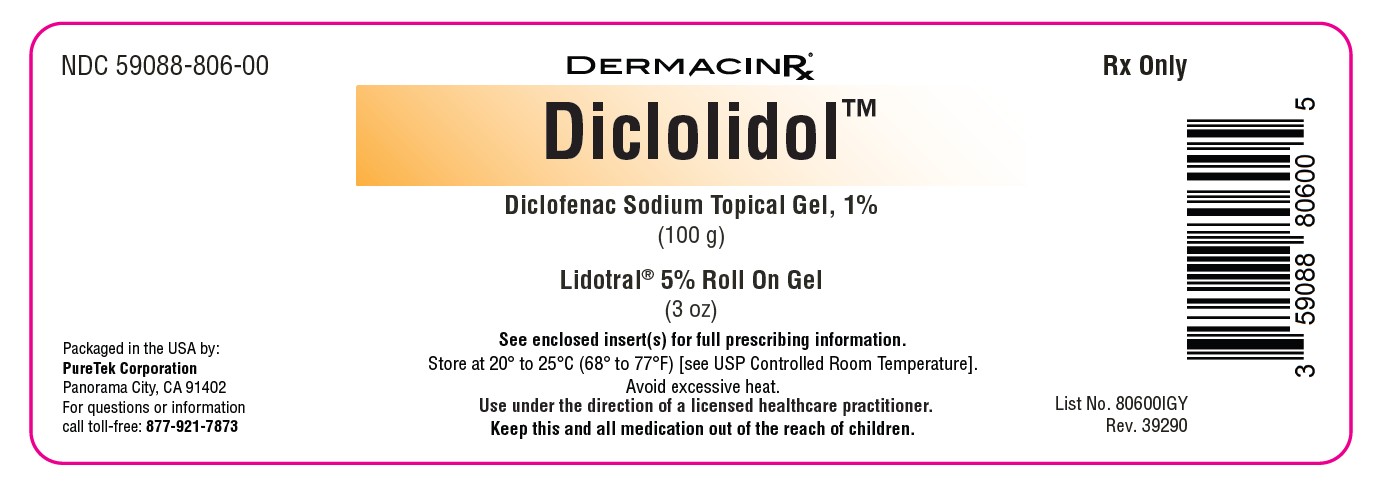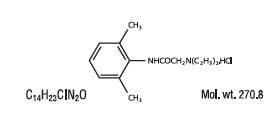 DRUG LABEL: Diclolidol Kit
NDC: 59088-806 | Form: KIT | Route: TOPICAL
Manufacturer: PureTek Corporation
Category: prescription | Type: HUMAN PRESCRIPTION DRUG LABEL
Date: 20250909

ACTIVE INGREDIENTS: LIDOCAINE HYDROCHLORIDE 50 mg/1 g; DICLOFENAC SODIUM 10 mg/1 g
INACTIVE INGREDIENTS: ARNICA MONTANA FLOWER; CYCLOMETHICONE 5; C30-45 ALKYL CETEARYL DIMETHICONE CROSSPOLYMER; CETETH-20 PHOSPHATE; AMINOMETHYLPROPANOL; DIHEXADECYL PHOSPHATE; CETOSTEARYL ALCOHOL; STEARETH-21; ALOE VERA LEAF; BENZYL ALCOHOL; GLYCERYL MONOSTEARATE; DIMETHICONE; ALCOHOL; GLYCERIN; ACRYLATES/C10-30 ALKYL ACRYLATE CROSSPOLYMER (60000 MPA.S AT 1.0%); WATER; EDETATE DISODIUM ANHYDROUS; AMMONIA; WATER; MINERAL OIL; POLYOXYL 20 CETOSTEARYL ETHER; CARBOMER HOMOPOLYMER TYPE C; COCO-CAPRYLATE/CAPRATE; ISOPROPYL ALCOHOL; PROPYLENE GLYCOL

NDC 59088-806-00
Diclolidol Kit
Lidotral 5% Roll On Gel (3oz) and Diclofenac Sodium 1% Topical Gel (100g)

Diclofenac Sodium 1% Topical Gel

Active ingredient: Diclofenac sodium (NSAID*) 1%

*nonsteroidal anti‑inflammatory drug

Inactive ingredients:

Carbomer Homopolymer Type C, Coco-Caprylate/caprate, Isopropyl Alcohol, Mineral Oil, Polyoxyl 20 Cetostearyl Ether, Propylene Glycol, Purified Water, Strong Ammonia Solution

Purpose:

Arthritis pain reliever

Indications:

For the temporary relief of arthritis pain ONLY in the following areas:

- hand, wrist, elbow (upper body areas)
- foot, ankle, knee (lower body areas)

this product may take up to 7 days to work for arthritis pain; it is not for immediate relief. If no pain relief in 7 days, stop use.

Directions:

These highlights do not include all the information needed to use Diclofenac Sodium 1% Topical Gel safely and effectively.

See full prescribing information for Diclofenac Sodium 1% Topical Gel.

Initial U.S. Approval: 1988

- Use up to 21 days unless directed by your doctor
- Not for strains, sprains, bruises or sports injuries. This product has not been shown to work for these types of injuries.

Daily for your arthritis pain:

- Use 4 times per day every day
- Do not use on more than 2 body areas at the same time

Per dose use ENCLOSED DOSING CARD to measure a dose.

- For each upper body area (hand, wrist, or elbow) – Squeeze out 2.25 inches (2 grams)
- For each lower body area (foot, ankle or knee) –Squeeze out 4.5 inches (4 grams)

Read the enclosed User Guidefor complete instructions:

- use only as directed
- do not use more than directed or for longer than directed
- apply only to clean, dry skin that does not have any cuts, open wounds, infections or rashes
- do not apply in same area as any other product
- do not apply with external heat such as heating pad
- do not apply a bandage over the treated area

store ENCLOSED DOSING CARD with your Diclofenac Sodium Topical Gel, 1% Arthritis Pain. The dosing card is re-usable.

Warnings: see full prescribing information for Diclofenac Sodium

For external use only

Allergy alert: Diclofenac may cause a severe allergic reaction, especially in people allergic to aspirin.
Symptoms may include:
• hives • asthma (wheezing) • skin reddening • blisters • facial swelling • shock • rash

If an allergic reaction occurs, stop use and seek medical help right away.
Liver warning: This product contains diclofenac. Liver damage may occur if you apply

- more or for a longer time than directed
- when using other drugs containing diclofenac

Stomach bleeding warning: This product contains an NSAID, which may cause severe stomach bleeding. The chance is small but higher if you

- are age 60 or older
- have had stomach ulcers or bleeding problems
- take a blood thinning (anticoagulant) or steroid drug
- take other drugs containing prescription or non-prescription NSAIDs (aspirin, ibuprofen, naproxen, or others)
- have 3 or more alcoholic drinks every day while using this product
- apply more or for longer than directed

Heart attack and stroke warning: NSAIDs, except aspirin, increase the risk of heart attack, heart failure, and stroke. These can be fatal. The risk is higher if you use more than directed or for longer than directed.

Do not use:

- if you have ever had an allergic reaction to any other pain reliever or to a fever reducer
- for strains, sprains, bruises or sports injuries. This product has not been shown to work for these types of injuries.
- right before or after heart surgery
- on more than 2 body areas at the same time
- in the eyes, nose or mouth

Ask a doctor before use if:

- you have problems or serious side effects from taking pain relievers or fever reducers
- stomach bleeding warning applies to you you have a history of stomach problems, such as heartburn
- you have high blood pressure, heart disease, liver cirrhosis, kidney disease, asthma, or had a stroke
- you are taking a diuretic
- you are under age 18 years. It is not known if this drug works or is safe in children under age 18 years.

Ask a doctor or pharmacist before use if you are:

- under a doctor’s care for any serious condition
- taking any other drug

When using this product:

- avoid contact with eyes, nose, or mouth
- if eye contact occurs, rinse thoroughly with water

Stop use and ask a doctor if:

- pain gets worse or lasts more than 21 days
- redness or swelling is present in the painful area
- fever occurs
- skin irritation occurs
- any new symptoms appear. These could be signs of a serious condition.
- you experience any of the following signs of stomach bleeding
- feel faint
- have bloody or black stools
- vomit blood
- have stomach pain that does not get better
- you have symptoms of heart problems or stroke
- chest pain
- trouble breathing
- leg swelling
- weakness in one part or side of body
- slurred speech

If pregnant or breast-feeding:

ask a health professional before use. It is especially important not to use diclofenac at 20 weeks or later in pregnancy unless definitely directed to do so by a doctor because it may cause problems in the unborn child or complications during delivery.

Keep out of reach of children:

If swallowed, get medical help or contact a Poison Control Center right away.

Other information:

- Store at 20-25 oC (68°F - 77°F). Keep from freezing.
- read all product information before using. Keep the dossing card, the carton and accompanying User guide for important information.

DESCRIPTION: Lidotral® 5% Roll on Gel

Lidotral® 5% Roll on Gel contains 50 mg of Lidocaine HCI per gram in a mild acidic vehicle with Acrylates/C10-30 Alkyl Acrylate Crosspolymer, Aloe Barbadensis (Aloe Vera) Leaf Juice, Aminomethyl Propanol, Aqua (Purified Water), Arnica Montana (Arnica) Flower Extract, Benzyl Alcohol, C30-45 Alkyl Cetearyl Dimethicone Crosspolymer, Cetearyl Alcohol, Ceteth-20 Phosphate, Cyclopentasiloxane, Dicetyl Phosphate, Dimethicone, Disodium EDTA, Ethyl Alcohol, Glycerin, Glyceryl Stearate, Steareth-21.

Lidocaine HCl is chemically designated as acetamide, 2-(diethylamino)-N-(2,6 dimethylphenyl), and has the following structure:

CLINICAL PHARMACOLOGY:

Mechanism of Action: Lidotral® 5% Roll on Gel releases lidocaine from a mild acidic vehicle to stabilize the neuronal membrane by inhibiting the ionic fluxes required for initiation and conduction of impulses, thereby effecting local anesthetic action. A mild acidic vehicle lowers pH to increase protection against alkaline irritants and to provide a favorable environment for healing.

Pharmacokinetics:

Lidocaine may be absorbed following topical administration to mucous membranes, its rate and extent of absorption depending upon the specific site of application, duration of exposure, concentration and total dosage. In general, the rate of absorption of local anesthetic agents following topical application occurs most rapidly after intratracheal administration. Lidocaine is also well-absorbed from the gastrointestinal tract, but little intact drug appears in the circulation because of biotransformation in the liver.

Lidocaine is metabolized rapidly by the liver and metabolites and unchanged drug are excreted by the kidneys. Biotransformation includes oxidative N-dealkylation, ring hydroxylation, cleavage of the amide linkage and conjugation. N-dealkylation, a major pathway of biotransformation, yields the metabolites monoethylglycinexylidide and glycinexylidide. The pharmacological/ toxicological actions of these metabolites are similar to, but less potent than, those of lidocaine. Approximately 90% of lidocaine administered is excreted in the form of various metabolites and less than 10% is excreted unchanged. The primary metabolite in urine is a conjugate of 4-hydroxy-2, 6-dimethylaniline. The plasma binding of lidocaine is dependent on drug concentration and the fraction bound decreases with increasing concentration. At concentrations of 1 to 4 g of free base per mL, 60 to 80 percent of lidocaine is protein bound. Binding is also dependent on the plasma concentration of the alpha-1-acid glycoprotein. Lidocaine crosses the blood-brain and placental barriers, presumably by passive diffusion. Studies of lidocaine metabolism following intravenous bolus injections have shown that the elimination half-life of this agent is typically 1.5 to 2 hours. Because of the rapid rate at which lidocaine is metabolized, any condition that affects liver function may alter lidocaine kinetics. The half-life may be prolonged two-fold or more in patients with liver dysfunction. Renal dysfunction does not affect lidocaine kinetics, but may increase the accumulation of metabolites. Factors such as acidosis and the use of CNS stimulants and depressants affect the CNS levels of lidocaine required to produce overt systemic effects. Objective adverse manifestations become increasingly apparent with increasing venous plasma levels above 6 g free base per mL. In the rhesus monkey, arterial blood levels of 18-21 g/mL have been shown to be threshold for convulsive activity.

INDICATIONS:

For the temporary relief of pain.

WARNINGS:

For external use only. Not for ophthalmic use.

PRECAUTIONS:

If irritation or sensitivity occurs or infection appears, discontinue use and institute appropriate therapy. Lidotral® 5% Roll on Gel should be used with caution in ill, elderly, debilitated patients and children who may be more sensitive to the systemic effects of lidocaine.

Carcinogenesis, Mutagenesis and Impairment of Fertility: Studies of lidocaine in animals to evaluate the carcinogenic and mutagenic potential of the effect on fertility have not been conducted.

Use in Pregnancy: Teratogenic Effects; Pregnancy Category B. Reproduction studies have been performed for lidocaine in rats at doses up to 6.6 times the human dose and have revealed no evidence of harm to the fetus caused by lidocaine. There are, however, no adequate and well-controlled studies in pregnant women. Animal reproduction studies are not always predictive of human response. General consideration should be given to this fact before administering lidocaine to women of childbearing potential, especially during early pregnancy when maximum organogenesis takes place.

Nursing Mothers: It is not known whether this drug is excreted in human milk. Because many drugs are excreted in human milk, caution should be exercised when this drug is administered to a nursing mother.

Pediatric Use: Dosage in pediatric patients would be reduced commensurate with age, body weight and physical condition.

CONTRAINDICATIONS:

Tuberculous or fungal lesions of skin vaccinia, varicella and acute herpes simplex and in persons who have shown hypersensitivity to any of its components. Lidocaine is contraindicated in patients with a known history of hypersensitivity to local anesthetics of the amide type.

ADVERSE REACTIONS:

During or immediately after treatment, the skin at the site of treatment may develop erythema or edema or may be the locus of abnormal sensation.

DOSAGE:

Adults and children 12 years of age and older: apply a thin film to the affected areas(s) two or three times per day or as directed by a licensed healthcare practitioner.

HOW SUPPLIED:

Lidotral® 5% Roll on Gel is supplied in a 3 oz. (85 g) roll on bottle (NDC 59088-327-07).

KEEP THIS AND ALL MEDICATIONS OUT OF THE REACH OF CHILDREN.
Store at 20º-25ºC (68º-77º F) [see USP Controlled Room Temperature]. Protect from freezing.

Diclolidol Kit Lidotral 5% Roll on Gel 3oz and Diclofenac Sodium 1% Gel 100g

Manufactured by:

PureTek Corporation

Panorama City, CA 91402

For questions or information call toll-free: 877-921-7873